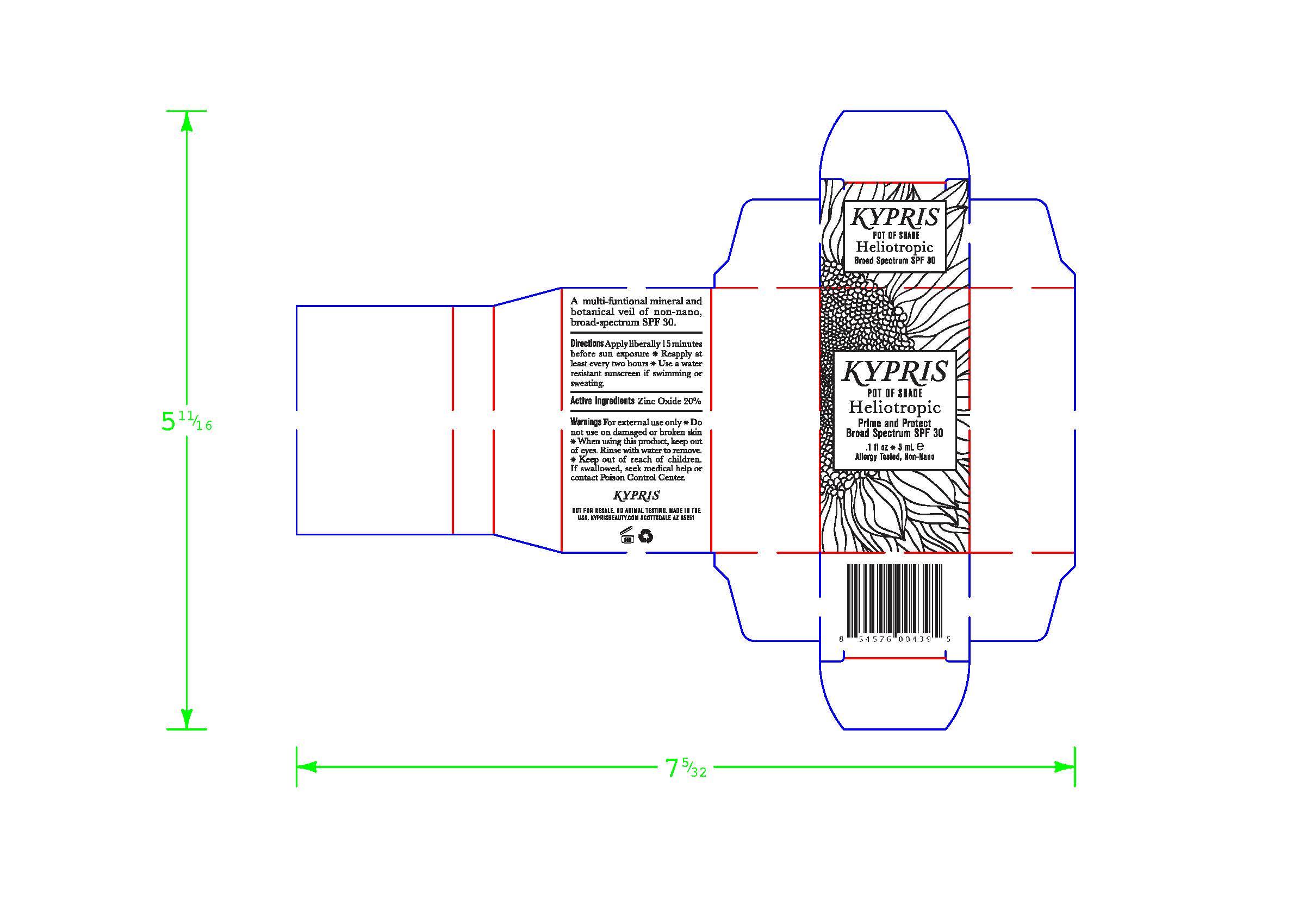 DRUG LABEL: Cream
NDC: 61354-030 | Form: CREAM
Manufacturer: Oxygen Development LLC
Category: otc | Type: HUMAN OTC DRUG LABEL
Date: 20230210

ACTIVE INGREDIENTS: ZINC OXIDE 19.72 mg/100 mg
INACTIVE INGREDIENTS: COCONUT ALKANES; WATER; MEDIUM-CHAIN TRIGLYCERIDES; ISOAMYL LAURATE; POLYHYDROXYSTEARIC ACID (2300 MW); SODIUM CHLORIDE; SILICON DIOXIDE; GLYCERYL CAPRYLATE; ISOSTEARIC ACID; ROSA X DAMASCENA FLOWER; SUNFLOWER OIL; POLYGLYCERYL-6 POLYRICINOLEATE; LECITHIN, SOYBEAN; POLYGLYCERYL-3 PENTARICINOLEATE; GLYCERIN

KYPRIS POT OF SHADE HELIOTROPIC PRIME AND PROTECT BROAD SPECTRUM SPF 30

Directions

Apply liberally 15 minutes before sun exposure.
Reapply at least every two hours
Use a water resistant sunscreen if swimming or sweating.

Active Ingredients

Zinc Oxide 20%

Warnings

For external use only.

Do not use on damaged on broken skin.

When using this product, keep out of eyes. Rinse with water to remove.

Keep out of reach of children. If swallowed, seek medical help or contact Poison Control Center.